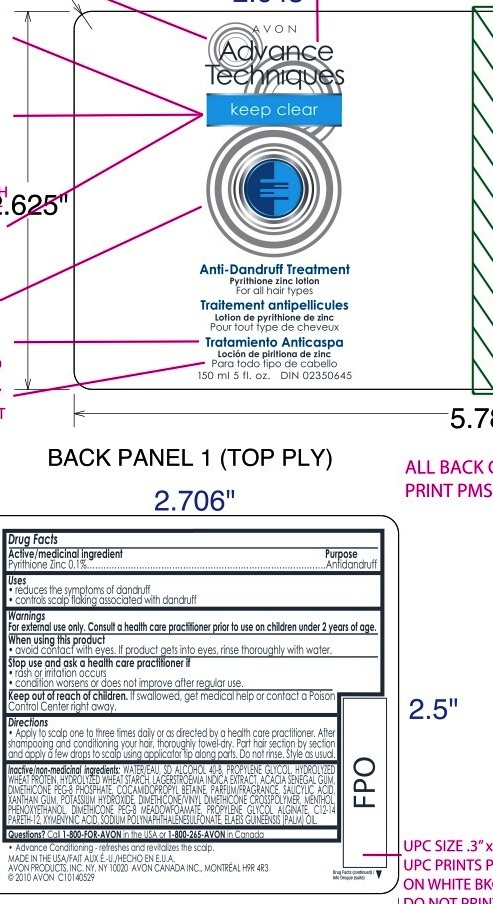 DRUG LABEL: Advance Techniques Keep Clear
NDC: 10096-0220 | Form: LOTION
Manufacturer: Avon Products, Inc.
Category: otc | Type: HUMAN OTC DRUG LABEL
Date: 20100611

ACTIVE INGREDIENTS: PYRITHIONE ZINC  0.15 mL/150 mL
INACTIVE INGREDIENTS: WATER; PROPYLENE GLYCOL; COCAMIDOPROPYL BETAINE; SALICYLIC ACID; POTASSIUM HYDROXIDE; MENTHOL; PHENOXYETHANOL; PROPYLENE GLYCOL ALGINATE

Drug Facts

Active/medicinal ingredient Purpose

Pyrithione Zinc 0.1%..........................................Antidandruff

Uses

- reduces the symptoms of dandruff
- controls scalp flaking associated with dandruff

Warnings

For external use only. Consult a health care practitioner prior to use on children under 2 years of age.

When using this product

- avoid contact with eyes. If product gets into eyes, rinse thoroughly with water.

ASK DOCTOR

Stop us and ask a health care practitioner if

- rash or irritation occurs
- condition worsens or does not improve after regular use.

Keep out of reach of children. If swallowed, get medical help or contact a Poison Control Center right away.

Directions

- Apply to scalp one to three times daily or as directed by a health care practitioner. After shampooing and conditioning your hair, thoroughly towel-dry. Part hair section by section and apply a few drops to scalp using applicator tip along parts. Do not rinse. Style as usual.

Inactive/non-medicinal ingredients:

WATER/EAU
SD ALCOHOL 40-B
PROPYLENE GLYCOL
HYDROLYZED WHEAT PROTEIN
HYDROLYZED WHEAT STARCH
LAGERSTROEMIA INDICA EXTRACT
ACACIA SENEGAL GUM
DIMETHICONE PEG-8 PHOSPHATE
COCAMIDOPROPYL BETAINE
PARFUM/FRAGRANCE
SALICYLIC ACID
XANTHAN GUM
POTASSIUM HYDROXIDE
DIMETHICONE/VINYL DIMETHICONE CROSSPOLYMER
MENTHOL
PHENOXYETHANOL
DIMETHICONE PEG-8 MEADOWFOAMATE
PROPYLENE GLYCOL ALGINATE
C12-14 PARETH-12
XYMENYNIC ACID
SODIUM POLYNAPHTHALENESULFONATE
ELAEIS GUINEENSIS (PALM) OIL

Questions? Call 1-800-FOR-AVON
or 1-800-265-AVON in Canada